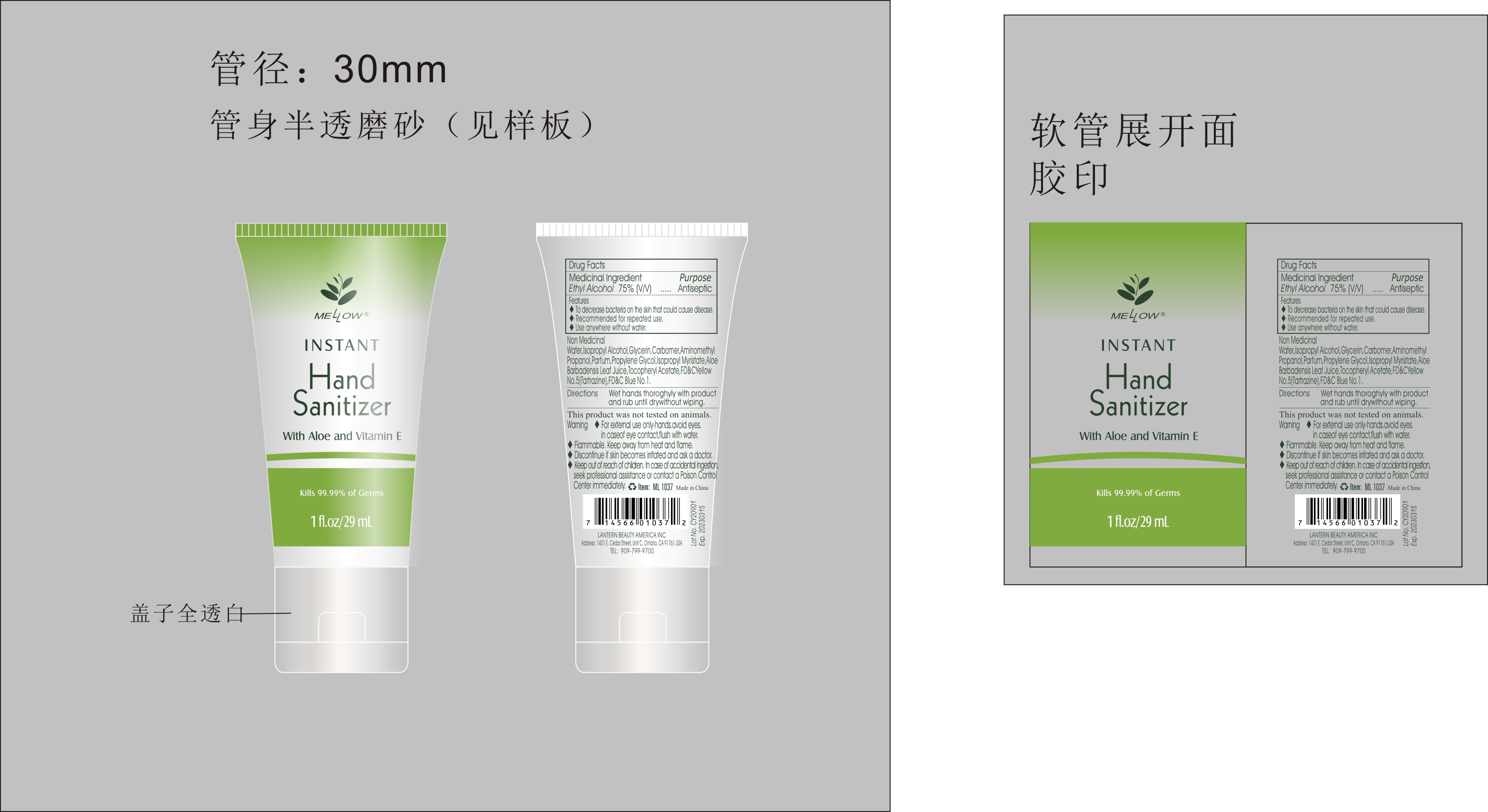 DRUG LABEL: Instant hand sanitizer with aloe and Vitamine E 29ml
NDC: 54860-395 | Form: LIQUID
Manufacturer: Shenzhen Lantern Scicence Co., Ltd.
Category: otc | Type: HUMAN OTC DRUG LABEL
Date: 20220425

ACTIVE INGREDIENTS: ALCOHOL 71 g/100 g
INACTIVE INGREDIENTS: ALOE VERA LEAF 0.1 g/100 g; PIGMENT BLUE 1 0.000008 g/100 g; PROPYLENE GLYCOL 0.1 g/100 g; ISOPROPYL MYRISTATE 0.001 g/100 g; ISOPROPYL ALCOHOL 0.5 g/100 g; .ALPHA.-TOCOPHEROL ACETATE 0.001 g/100 g; ALOE 0.2 g/100 g; AMINOMETHYLPROPANOL 0.14 g/100 g; WATER 27.057972 g/100 g; GLYCERIN 0.5 g/100 g; BASIC YELLOW 5 0.00002 g/100 g

Instant hand sanitizer with aloe and Vitamin E 29mL

Medicical Ingredient

Medicical Ingredient Purpose

Ethyl Alcohol 75%（V/V） Antiseptic

Features

To decrease bacteria on the skin that could cause disease.

DOSAGE AND ADMINISTRATION

Recommended for repeated use.

use anywhere without water.

Warning

For external use only-hands.avoid eyes.in case of eye contact,flush with water.

Flammable,keep away from heat and flame.

Discontinue if skin becomes irritated and ask a doctor.

Keep out of reach of children,In case of accidental ingestion,seek professional assistance or contact a Poison control center immediately.

WARNINGS AND PRECAUTIONS

For external use only.

Flammable, keep away from heat and flame.

STOP USE

Discontinue if skin becomes irritated and ask a doctor .

Keep out of reach of children. In case of accidental ingestion, seek professional assistance or contact a poson control center immediately.

Non-Medicinal

Alcohol，Aqua(water)，Isopropyl Alcohol，Glycerin，Carbomer，Aminomethyl Propanol，Parfum，Propylene Glycol，ISOPROPYL MYRISTATE，ALOE BARBADENSIS LEAF JUICE，Tocopheryl Acetate，YELLOW 5，BLUE 1.

Directions

Wet hands thoroughly with product and rub until dry without wiping

For children under 6, use only under adult supervision.

Not recommended for infants.

When using this product

keep out of eyes. In case of contact with eyes, flush thoroughly with water.

Do not inhale or ingest.

Avoid contact with broken skin.

Other information

Do not store above 105F.

May discolor some fabrics.

Harmful to wood finishes and plastics.